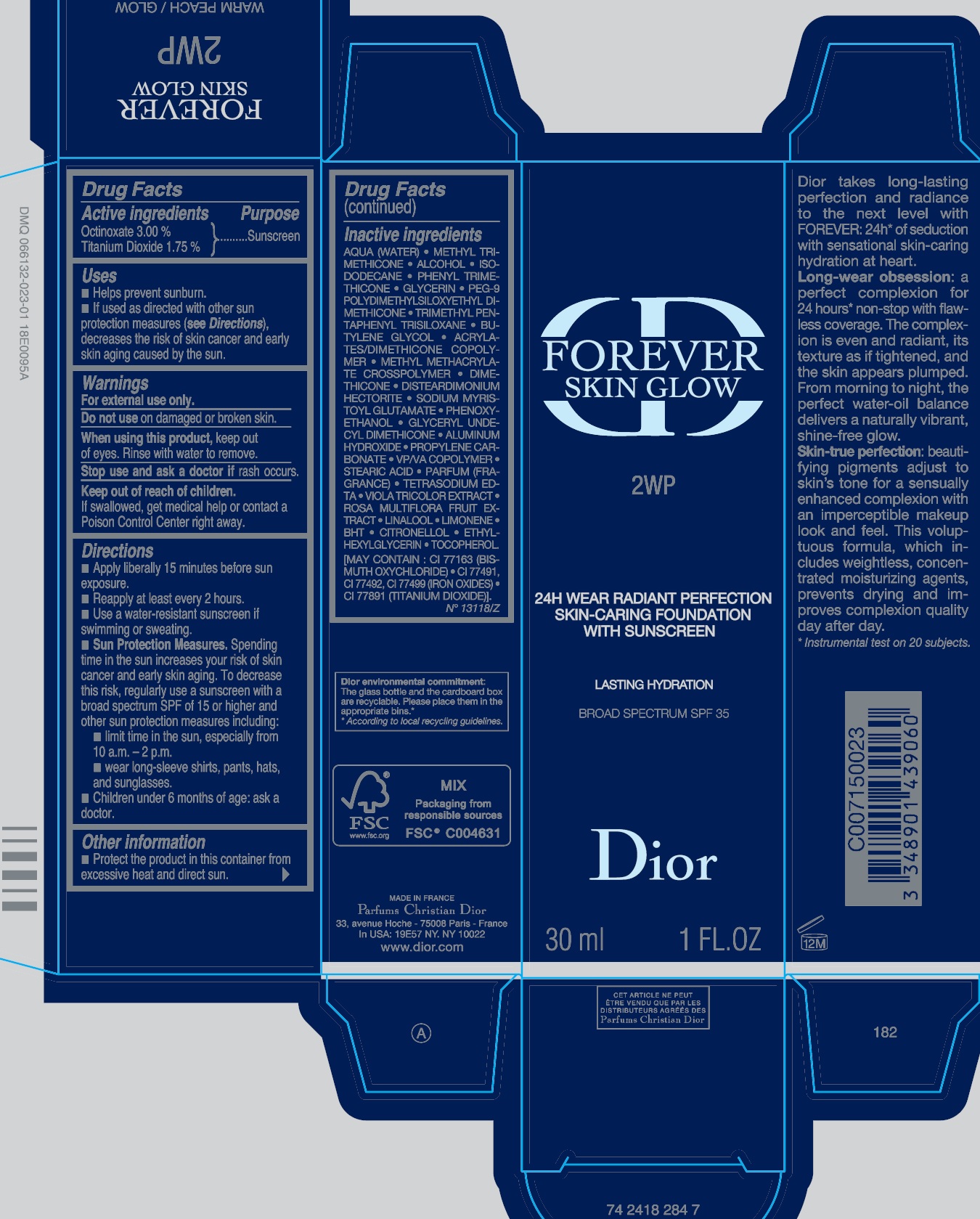 DRUG LABEL: 
                  FOREVER SKIN GLOW 24h Wear Radiant Perfection Skin Caring Foundation With Sunscreen BROAD SPECTRUM SPF 35 Lasting Hydration
                
                  

NDC: 61957-2921 | Form: EMULSION
Manufacturer: PARFUMS CHRISTIAN DIOR
Category: otc | Type: HUMAN OTC DRUG LABEL
Date: 20231103

ACTIVE INGREDIENTS: OCTINOXATE 30 mg/1 mL; TITANIUM DIOXIDE 17.5 mg/1 mL
INACTIVE INGREDIENTS: WATER; METHYL TRIMETHICONE; ALCOHOL; ISODODECANE; PHENYL TRIMETHICONE; GLYCERIN; PEG-9 POLYDIMETHYLSILOXYETHYL DIMETHICONE; TRIMETHYL PENTAPHENYL TRISILOXANE; BUTYLENE GLYCOL; METHYL METHACRYLATE/GLYCOL DIMETHACRYLATE CROSSPOLYMER; DIMETHICONE; DISTEARDIMONIUM HECTORITE; SODIUM MYRISTOYL GLUTAMATE; PHENOXYETHANOL; ALUMINUM HYDROXIDE; PROPYLENE CARBONATE; STEARIC ACID; EDETATE SODIUM; LINALOOL, (+/-)-; BUTYLATED HYDROXYTOLUENE; .BETA.-CITRONELLOL, (R)-; ETHYLHEXYLGLYCERIN; TOCOPHEROL

FOREVER SKIN GLOW 24h Wear Radiant Perfection Skin-Caring Foundation With Sunscreen BROAD SPECTRUM SPF 35 Lasting Hydration 2WP

Active ingredients

Octinoxate 3.00%

Titanium Dioxide 1.75%

Purpose

Sunscreen

Uses

- Helps prevent sunburn.
- If used as directed with other sun protection measures (), decreases the risk of skin cancer and early skin aging caused by the sun. see Directions

Warnings

For external use only.

Do not use

on damaged or broken skin.

When using this product,

keep out of eyes. Rinse with water to remove.

Stop use and ask a doctor if

rash occurs.

Keep out of reach of children.

If swallowed, get medical help or contact a Poison Control Center right away.

Directions

- Apply liberally 15 minutes before sun exposure.
- Reapply at least every 2 hours.
- Use a water-resistant sunscreen if swimming or sweating.
- Spending time in the sun increases your risk of skin cancer and early skin aging. To decrease this risk, regularly use a sunscreen with a broad spectrum SPF of 15 or higher and other sun protection measures including: Sun Protection Measures.
- limit time in the sun, especially from 10 a.m. - 2 p.m.
- wear long-sleeve shirts, pants, hats, and sunglasses.
- Children under 6 months of age: ask a doctor.

Other information

- Protect the product in this container from excessive heat and direct sun.

Inactive ingredients

AQUA (WATER), METHYL TRIMETHICONE, ALCOHOL, ISODODECANE, PHENYL TRIMETHICONE, GLYCERIN, PEG-9 POLYDIMETHYLSILOXYETHYL DIMETHICONE, TRIMETHYL PENTAPHENYL TRISILOXANE, BUTYLENE GLYCOL, ACRYLATES/DIMETHICONE COPOLYMER, METHYL METHACRYLATE CROSSPOLYMER, DIMETHICONE, DISTEARDIMONIUM HECTORITE, SODIUM MYRISTOYL GLUTAMATE, PHENOXYETHANOL, GLYCERYL UNDECYL DIMETHICONE, ALUMINUM HYDROXIDE, PROPYLENE CARBONATE, VP/VA COPOLYMER, STEARIC ACID, PARFUM (FRAGRANCE), TETRASODIUM EDTA, VIOLA TRICOLOR EXTRACT, ROSA MULTIFLORA FRUIT EXTRACT, LINALOOL, LIMONENE, BHT, CITRONELLOL, ETHYL HEXYGLYCERIN, TOCOPHEROL. [MAY CONTAIN : CI 77163 (BISMUTH OXYCHLORIDE), CI 77491, CI 77492, CI 77499 (IRON OXIDES), CI 77891 (TITANIUM DIOXIDE)].